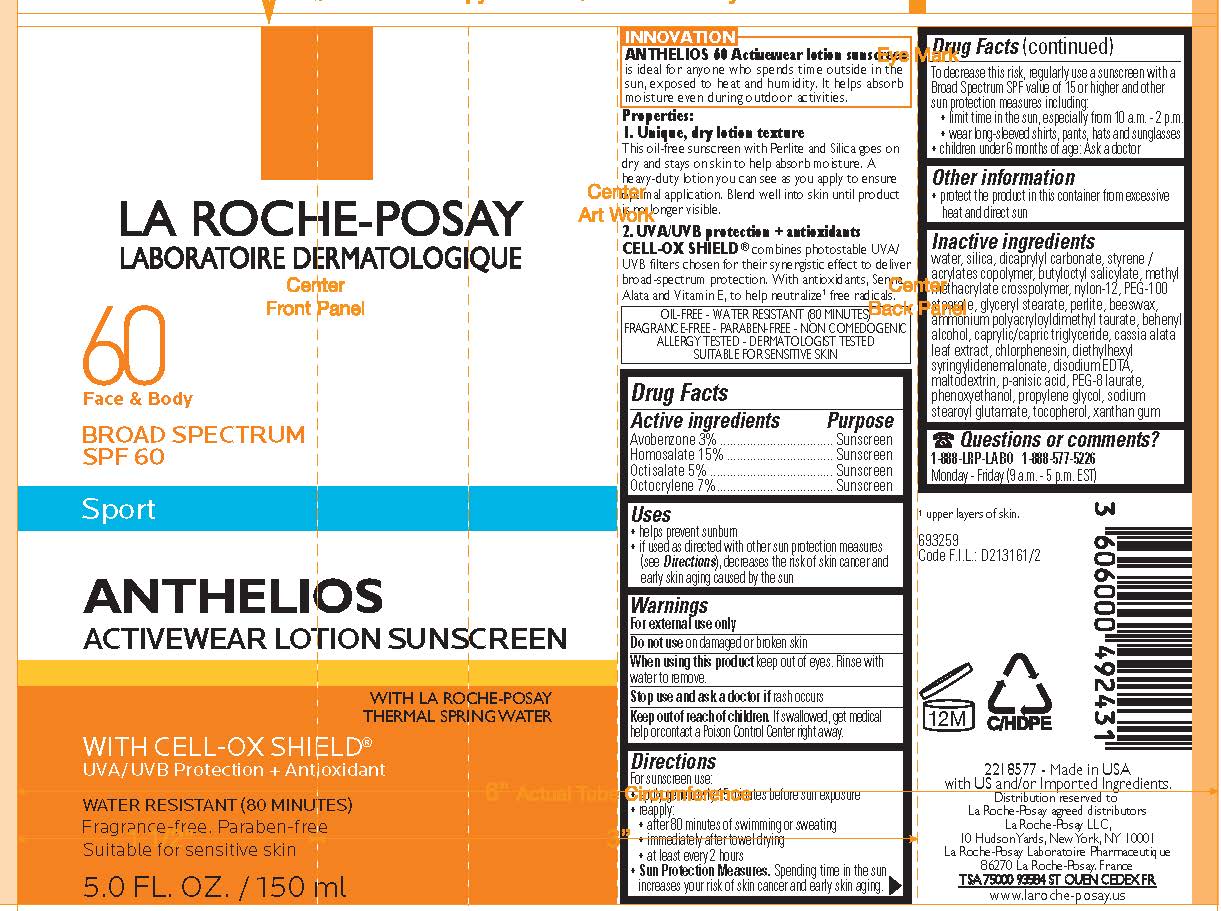 DRUG LABEL: La Roche Posay Laboratoire Dermatologique Sport Anthelios Activewear Broad Spectrum SPF 60 Sunscreen
NDC: 49967-431 | Form: LOTION
Manufacturer: L'Oreal USA Products Inc
Category: otc | Type: HUMAN OTC DRUG LABEL
Date: 20231231

ACTIVE INGREDIENTS: AVOBENZONE 30 mg/1 mL; HOMOSALATE 150 mg/1 mL; OCTISALATE 50 mg/1 mL; OCTOCRYLENE 70 mg/1 mL
INACTIVE INGREDIENTS: WATER; NYLON-12; GLYCERYL STEARATE SE; PERLITE; CHLORPHENESIN; MALTODEXTRIN; PEG-8 LAURATE; PHENOXYETHANOL; PROPYLENE GLYCOL; SODIUM STEAROYL GLUTAMATE; TOCOPHEROL; XANTHAN GUM

Drug Facts

Active ingredients

Avobenzone 3%

Homosalate 15%

Octisalate 5%

Octocrylene 7%

Purpose

Sunscreen

Uses

- helps prevent sunburn
- if used as directed with other sun protection measures (see Directions), decreases the risk of skin cancer and early skin aging caused by the sun

Warnings

For external use only

Do not use

on damaged or broken skin

When using this product

keep out of eyes. Rinse with water to remove.

Stop use and ask a doctor if

rash occurs

Keep out of reach of children.

If swallowed, get medical help or contact a Poison Control Center right away.

Directions

- apply generously 15 minutes before sun exposure
- reapply:
- after 80 minutes of swimming or sweating
- immediately fter towel drying
- at least every 2 hours
- Sun Protection Measures. Spending time in the sun increases your risk of skin cancer and early skin aging. To decrease this risk, regularly use a sunscreen with a Broad Spectrum SOF calue of 15 or higher and other sun protection measures including:
- limit time in the sun, especially between 10 a.m. and 2 p.m.
- wear long-sleeved shirts, pants, hats and sunglasses
- children under 6 months of age: ask a doctor

Other information

protect the product in this container from excessive heat and direct sun

Inactive ingredients

water, silica, dicaprylyl carbonate, styrene/acrylates copolymer, butyloctyl salicylate, menthyl methacrylae crosspolymer, nylon-12, PEG-100, glyceryl stearate, perlite, beeswax, ammonium poolyacrylloyldiimethy taurate, behenyl alcohol, caprylic/capric triglyceride, cassia alata leaf extract, chlorphenesisn, diethylhexyl syringlyidenemalonate, disodium EDTA, maltodextrin, p-anisic acid, PEG-8 laurate, phenoxethanol, propylene glycol, sodium stearoyl glutamate, tocopherol, xanthan gum

Questions or comments?

1-888-577-5226 Monday - Friday (9 a.m. - 5 p.m. EST)